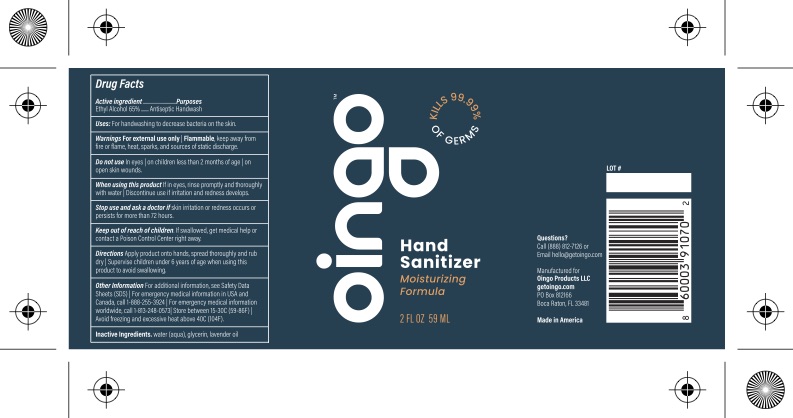 DRUG LABEL: Hand Sanitizer
NDC: 79436-102 | Form: SPRAY
Manufacturer: Oingo Products LLC
Category: otc | Type: HUMAN OTC DRUG LABEL
Date: 20200819

ACTIVE INGREDIENTS: ALCOHOL 65 mL/100 mL
INACTIVE INGREDIENTS: WATER; LAVENDER OIL; GLYCERIN

Active Ingredient(s)

Alcohol 65% v/v. Purpose: Antiseptic

Purpose

Antiseptic, Hand Sanitizer

Use

for handwashing to decrease bacteria on the skin

Warnings

For external use only, Flammable, keep away from fire or flame, heat, sparks, and sources of static discharge

Do not use

- In eyes | on children less than 2 months of age | on open skin wounds

When using this product

If in eyes, rinse promptly and thoroughly with water | Discontinue use if irritation and redness develops

Stop use and ask a doctor

If skin irritation or redness occurs or persists for more than 72 hours.

Keep out of reach of children.

If swallowed, get medical help or contact a Poison Control Center right away.

Directions

- Place enough product on hands to cover all surfaces. Rub hands together until dry.
- Supervise children under 6 years of age when using this product to avoid swallowing.

Other information

For additional information, see Safety Data
Sheets (SDS) | For emergency medical information in USA and
Canada, call 1-888-255-3924 | Store between 15-
30C (59-86F) | Avoid freexing and excessive heat above 40C
(104F)

Inactive ingredients

water (aqua), propylene glycol,
dimethicone PEG-7 Isostearate, acrylates/ C10-30 Alkyl
Acrylate Crosspolymer, aminomethylpropanediol, tocopherol
acetate, aloe barbadensis leaf juice

Package Label - Principal Display Panel

59 mL NDC: 79436-102-01